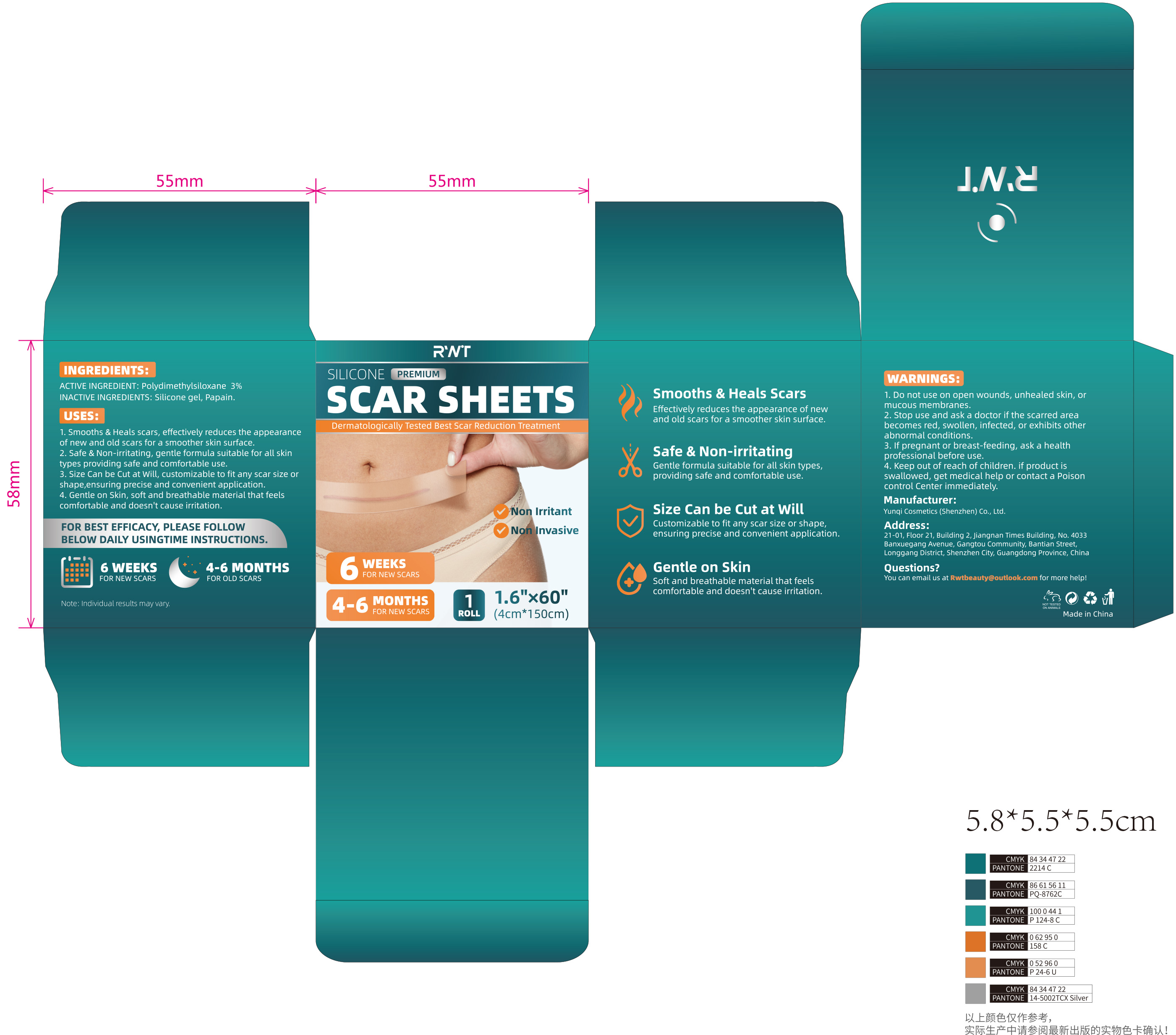 DRUG LABEL: SCAR SHEETS
NDC: 84763-001 | Form: TAPE
Manufacturer: Yunqi Cosmetics (Shenzhen) Co., Ltd
Category: otc | Type: HUMAN OTC DRUG LABEL
Date: 20240917

ACTIVE INGREDIENTS: DIMETHICONE, UNSPECIFIED 0.03 g/1 1
INACTIVE INGREDIENTS: SILICON DIOXIDE; PAPAIN

SCAR SHEETS

ACTIVE INGREDIENT

Polydimethylsiloxane 3%

PURPOSE

Smooths & Heals ScarsEffectively reduces the appearance of newand old scars for a smoother skin surface.

Keep out of reach of children. if product isswallowed, get medical help or contact a Poisoncontrol centerimmediately

INDICATIONS AND USAGE

1.Smooths & Heals scars, effectively reduces the appearanceof new and old scars for a smoother skin surface.
2. Safe & Non-irritating, gentle formula suitable for all skintypes providing safe and comfortable use.
3. Size Can be Cut at Will, customizable to fit any scar size orshape,ensuring precise and convenient application.
4. Gentle on Skin, soft and breathable material that feelscomfortable and doesn't cause irritation.

WARNINGS

1. Do not use on open wounds, unhealed skin, ormucous membranes.
2. Stop use and ask a doctor if the scarred areabecomes red,swollen,infected, or exhibits otherabnormal conditions.
3. lf pregnant or breast-feeding, ask a healthprofessional before use.
4. Keep out of reach of children. if product isswallowed,get medical help or contact a Poisoncontrol Center immediately.

DOSAGE AND ADMINISTRATION

Safe & Non-irritatingGentle formula suitable for all skin types,providing safe and comfortable use.

INACTIVE INGREDIENT

Silicone gel
Papain